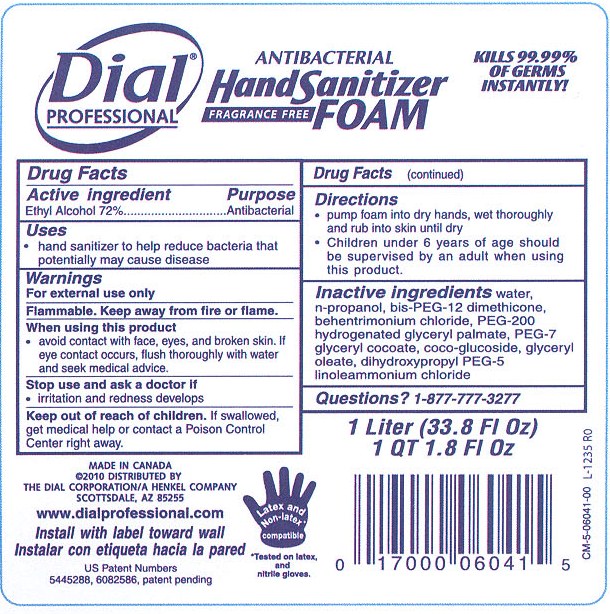 DRUG LABEL: Dial Professional Antibacterial Hand Sanitizer 
NDC: 54340-107 | Form: LIQUID
Manufacturer: The Dial Corporation
Category: otc | Type: HUMAN OTC DRUG LABEL
Date: 20110316

ACTIVE INGREDIENTS: Alcohol 72 mL/100 mL
INACTIVE INGREDIENTS: WATER; DIHYDROXYPROPYL PEG-5 LINOLEAMMONIUM CHLORIDE    ; PROPYL ALCOHOL; BEHENTRIMONIUM CHLORIDE

Drug Facts

Active ingredient

Ethyl Alcohol 72%

Purpose

Antibacterial

Uses

hand sanitizer to help reduce bacteria that potentially may cause disease

Warnings

For external use only

Flammable. Keep away from fire or flame.

When using this product

avoid contact with face, eyes, and broken skin. If eye contact occurs, flush thoroughly with water and seek medical advice.

Stop use and ask a doctor if

irritation and redness develops

Keep out of reach of children. If swallowed, get medical help or contact a Poison Control Center right away.

Directions

pump foam into dry hands, wet thoroughly and rub into skin until dry

Children under 6 years of age should be supervised by an adult when using this product.

Inactive ingredients

water, n-propanol, bis-PEG-12 dimethicone, behentrimonium chloride, PEG-200 hydrogenated glyceryl palmate, PEG-7 glyceryl cocoate, coco-glucoside, glyceryl linoleammonium chloride

Questions?

1-877-777-3277

PACKAGE LABEL

Dial Professional

Antibacterial Hand Sanitizer Fragrance Free Foam

Kills 99.99% of germs instantly

Made in Canada

2010 Distributed by The Dial Corporation/A Henkel Company

Scottsdale, AZ 85255

www.dialprofessional.com

Install with label toward wall

Instalar con etiqueta hacia la pared

US Patent Numbers

5445288, 6082586, patent pending

1 Liter (33.8 Fl Oz)

1 QT 1.8 Fl Oz

Latex and Non-latex compatible

Tested on latex and nitrile gloves.